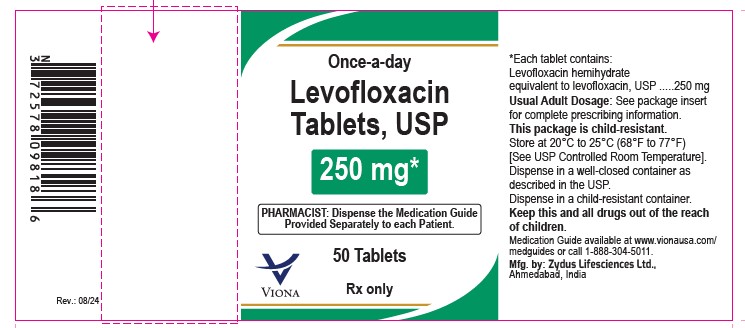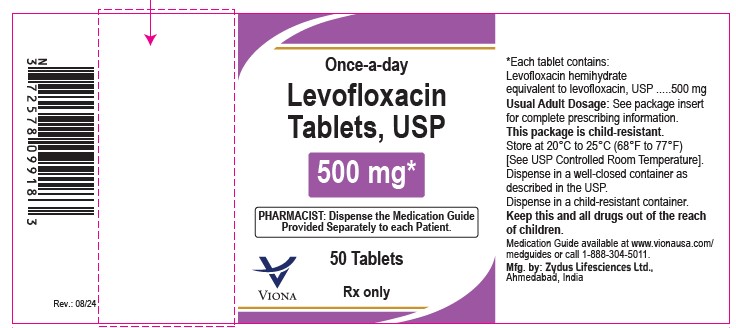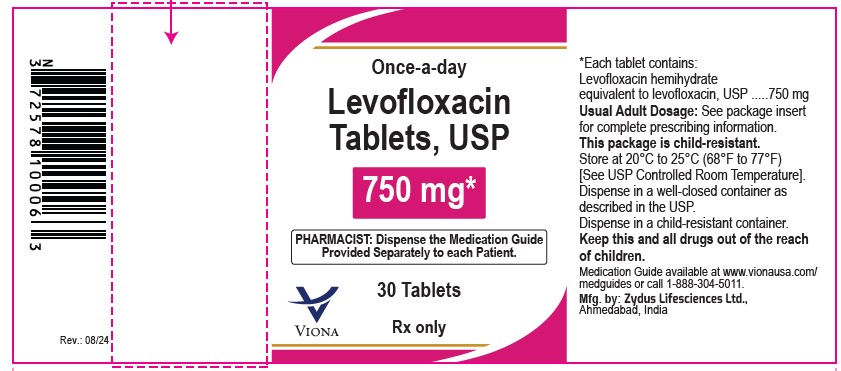 DRUG LABEL: levofloxacin
NDC: 65841-691 | Form: TABLET, FILM COATED
Manufacturer: Zydus Lifesciences Limited
Category: prescription | Type: HUMAN PRESCRIPTION DRUG LABEL
Date: 20240816

ACTIVE INGREDIENTS: LEVOFLOXACIN 250 mg/1 1
INACTIVE INGREDIENTS: CROSPOVIDONE (15 MPA.S AT 5%); HYPROMELLOSES; MAGNESIUM STEARATE; POLYETHYLENE GLYCOL 6000; TALC; TITANIUM DIOXIDE; CELLULOSE, MICROCRYSTALLINE

LEVOFLOXACIN TABLETS

PACKAGE LABEL.PRINCIPAL DISPLAY PANEL

NDC 65841-691-18 in bottle of 50 tablets

Levofloxacin Tablets USP, 250 mg

Rx only

50 tablets

NDC 65841-692-18 in bottle of 50 tablets

Levofloxacin Tablets USP, 500 mg

Rx only

50 tablets

NDC 65841-693-06 in bottle of 30 tablets

Levofloxacin Tablets USP, 750 mg

Rx only

30 tablets